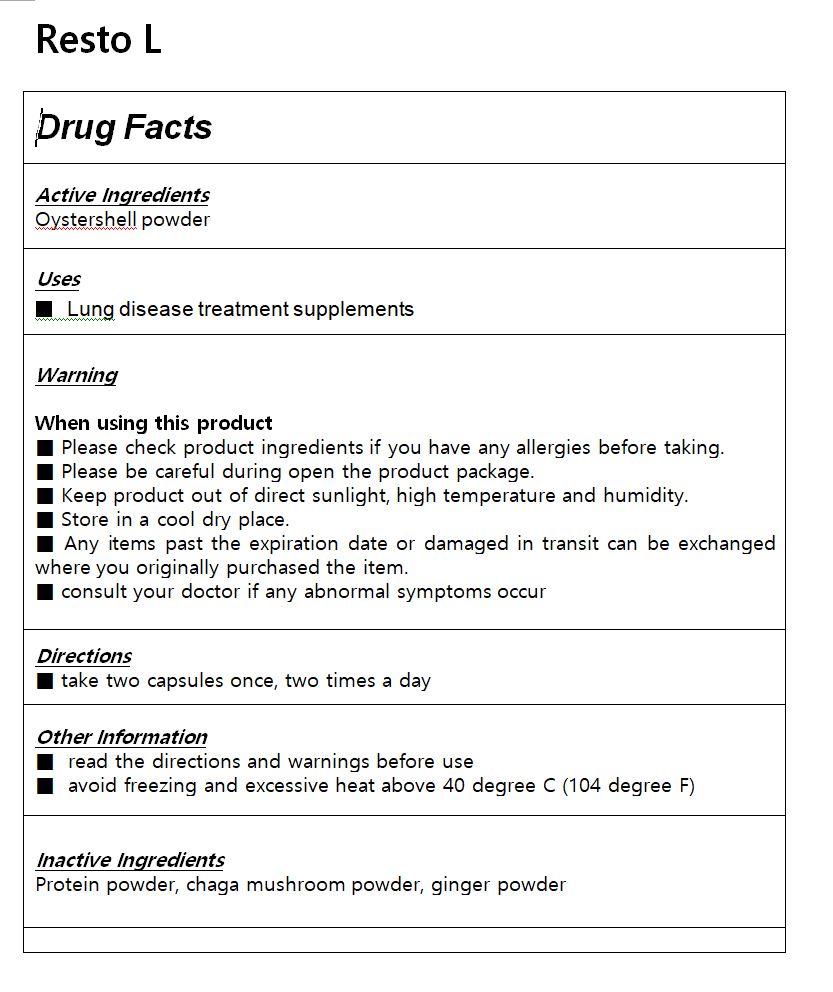 DRUG LABEL: Resto L
NDC: 81445-0006 | Form: TABLET
Manufacturer: coexleaders co.,ltd.
Category: otc | Type: HUMAN OTC DRUG LABEL
Date: 20210304

ACTIVE INGREDIENTS: CALCIUM 0.71 1/1 1
INACTIVE INGREDIENTS: GINGER

ACTIVE INGREDIENT

Oystershell powder

INACTIVE INGREDIENT

Protein powder, chaga mushroom powder, ginger powder

PURPOSE

Lung disease treatment supplements

KEEP OUT OF REACH OF CHILDREN

WARNING

Please check product ingredients if you have any allergies before taking.

Please be careful during open the product package.

Keep product out of direct sunlight, high temperature and humidity.

Store in a cool dry place.

Any items past the expiration date or damaged in transit can be exchanged where you originally purchased the item.

consult your doctor if any abnormal symptoms occur

USES

for oral use only

INDICATION & USAGE SECTION

take two capsules once, two times a day